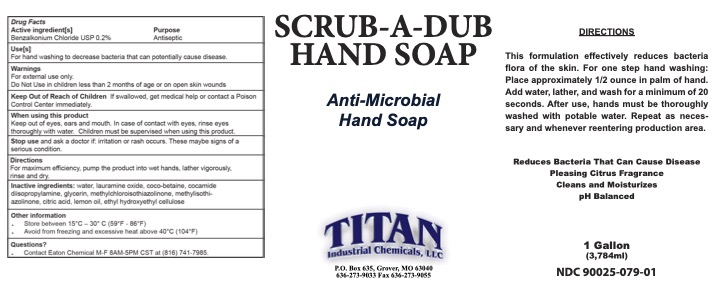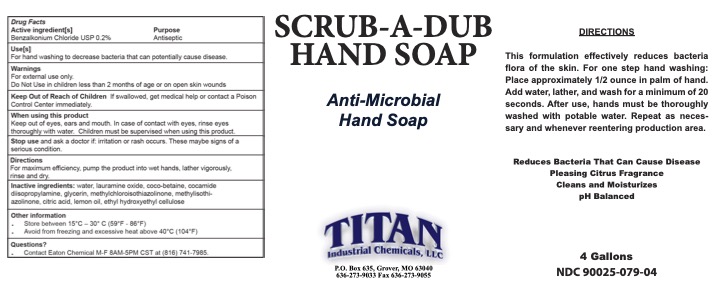 DRUG LABEL: SCRUB-A-DUB
NDC: 90025-079 | Form: SOAP
Manufacturer: TITAN INDUSTRIAL CHEMICALS, LLC
Category: otc | Type: HUMAN OTC DRUG LABEL
Date: 20211007

ACTIVE INGREDIENTS: BENZALKONIUM CHLORIDE 0.2 g/100 g
INACTIVE INGREDIENTS: HYDROXYETHYL CELLULOSE (5000 MPA.S AT 1%); COCO-BETAINE; COCO DIISOPROPANOLAMIDE; LAURAMINE OXIDE; GLYCERIN; METHYLCHLOROISOTHIAZOLINONE/METHYLISOTHIAZOLINONE MIXTURE; WATER; LEMON OIL; CITRIC ACID MONOHYDRATE

SCRUB-A-DUB

ACTIVE INGREDIENT

Benzalkonium Chloride 0.2%

KEEP OUT OF REACH OF CHILDREN

If swallowed, get medical help or contact a Poison Control Center immediately.

INACTIVE INGREDIENT

water, lauramine oxide, coco-betaine, cocamide diisopropylamine, glycerin, methylchloroisothiazolinone, methylisothi- azolinone, citric acid, lemon oil, ethyl hydroxyethyl cellulose

DOSAGE AND ADMINISTRATION

For maximum efficiency, pump the product into wet hands, lather vigorously, sinse and dry.

INDICATIONS AND USAGE

For hand washing to decrease bacteria that can potentially cause disease.

WARNINGS

For external use only.
Do Not Use in children less than 2 months of age or on open skin wounds

OTHER SAFETY INFORMATION

. Store between 15°C – 30° C (59°F - 86°F)

. Avoid from freezing and excessive heat above 40°C (104°F)

PURPOSE

Antiseptic